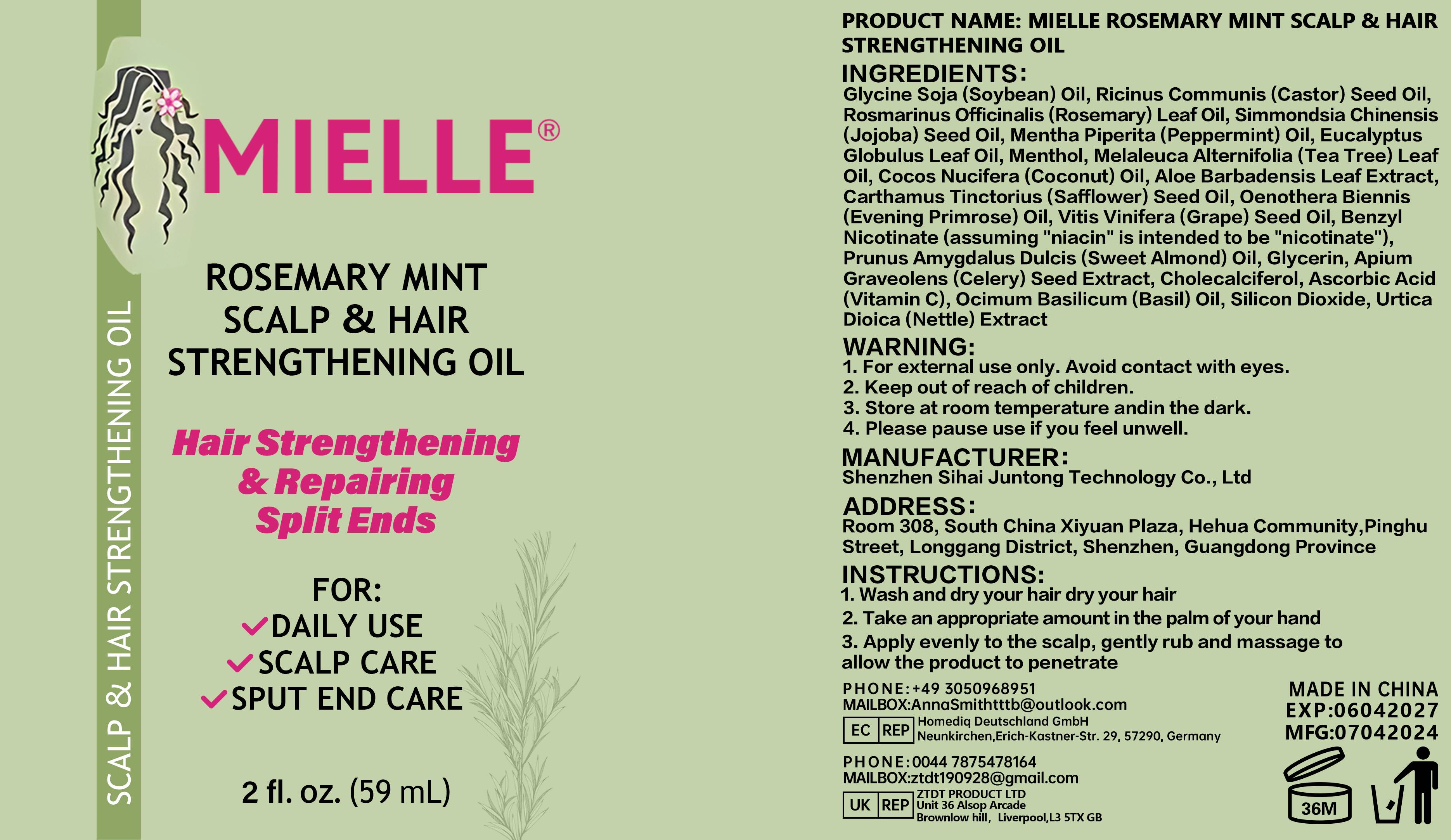 DRUG LABEL: MIELLEROSEMARYMINTSCALPHAIRSTRENGTHENINGOIL
NDC: 84350-022 | Form: LIQUID
Manufacturer: Shenzhen Sihai Juntong Technology Co., Ltd
Category: otc | Type: HUMAN OTC DRUG LABEL
Date: 20240829

ACTIVE INGREDIENTS: ASCORBIC ACID 1 g/100 mg
INACTIVE INGREDIENTS: WATER

ACTIVE INGREDIENT

Ricinus Communis (Castor) Seed Oil 5%

INACTIVE INGREDIENT

Water 5%

PURPOSE

moisturizing

WARNINGS

WARNING:1. For external use only. Avoid contact with eyes2. Keep out of reach of children.3. Store at room temperature andin the dark.4. Please pause use if you feel unwell.

Do not use

If you have allergic reactions, stop to use

when using this product

INSTRUCTIONS:1. Wash and dry your hair dry your hair2. Take an appropriate amount in the palm of your hand3.Apply evenly to the scalp, gently rub and massage toallow the product to penetrate

Keep out of reach of children

use

INSTRUCTIONS:1. Wash and dry your hair dry your hair2.Take an appropriate amount in the palm of your hand3. Apply evenly to the scalp, gently rub and massage toallow the product to penetrate

Dosage and administration

appropriate amount

PRINCIPAL DISPLAY PANEL

59ml NDC:84350-022-08